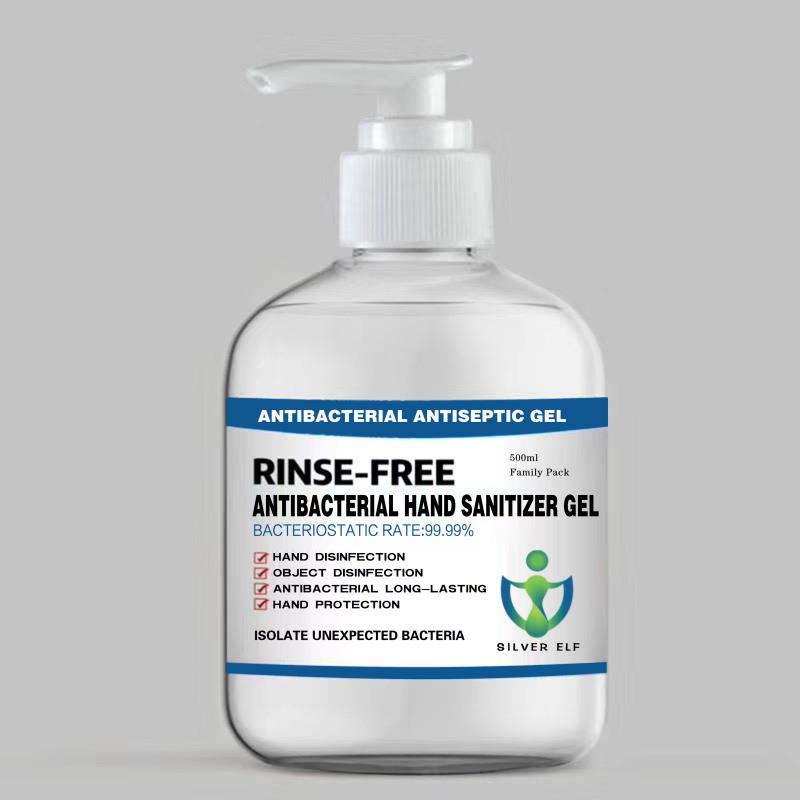 DRUG LABEL: Hand Sanitizer Gel(Ag)
NDC: 54039-001 | Form: GEL
Manufacturer: Anhui Wanxing Industry Co.,Ltd.
Category: homeopathic | Type: HUMAN OTC DRUG LABEL
Date: 20200512

ACTIVE INGREDIENTS: SILVER CATION 10 g/500 mL
INACTIVE INGREDIENTS: GLYCERYL MONOSTEARATE; HYDROXYETHYL CELLULOSE, UNSPECIFIED; .ALPHA.-TOCOPHEROL; METHYL BENZOATE

DOSAGE AND ADMINISTRATION

Keep tightly closed in a cool.dark,dry place.

INACTIVE INGREDIENT

Vitamin

Glyceryl stearate

Hydroxyethyl cellulose

Essence

INDICATIONS AND USAGE

jput Proper Amount Of The Hand Sanitizer lnto Your Palm And Gently Rub it Over Your Palms,ths Back Of Your Hands,fingers And The Spaces Between your Fingers,rub Your Hands Together Continuously Until They Are Dry

ACTIVE INGREDIENT

Silver ions

keep out of reach of children

PURPOSE

Disinfection
Sterilization
No Rinseing

WARNINGS

1.This product is for external use only,Do not take it internally.

2.Keep out of reach of children.